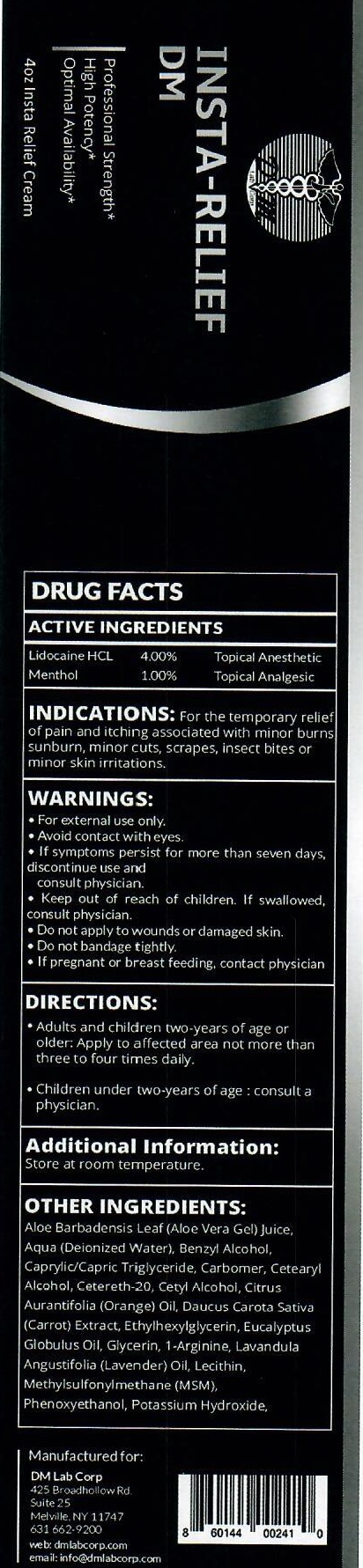 DRUG LABEL: INSTA RELIEF DM
NDC: 72465-600 | Form: CREAM
Manufacturer: DM LAB CORP
Category: otc | Type: HUMAN OTC DRUG LABEL
Date: 20231105

ACTIVE INGREDIENTS: LIDOCAINE HYDROCHLORIDE 40 mg/1 mL; MENTHOL 10 mg/1 mL
INACTIVE INGREDIENTS: ALOE VERA LEAF; WATER; BENZYL ALCOHOL; MEDIUM-CHAIN TRIGLYCERIDES; CARBOXYPOLYMETHYLENE; CETOSTEARYL ALCOHOL; POLYOXYL 20 CETOSTEARYL ETHER; CETYL ALCOHOL; LIME OIL; CARROT; ETHYLHEXYLGLYCERIN; EUCALYPTUS OIL; GLYCERIN; LAVENDER OIL; DIMETHYL SULFONE; PHENOXYETHANOL; POTASSIUM HYDROXIDE

INSTA-RELIEF DM

ACTIVE INGREDIENTS

Lidocaine HCL 4.00%

Menthol 1.00%

PURPOSE

Topical Anesthetic

INDICATIONS:

For the temporary relief of pain and itching assoicated with minor burns sunburn, minor cuts, scrapes, insect bites or minor skin irritations.

WARNINGS

- For external use only.
- Avoid contact with eyes.
- If symptoms persist for more than seven days, discontinue use and consult physician.

Keep out of reach of children.

If swallowed, consult physician.

Do not apply

- to wounds or damaged skin.
- Do not bandage tightly.

If pregnant or breast feeding,

contact physician

DIRECTIONS:

- Adults and children two-years of age or older: Apply to affected area not more than three to four times daily
- Children under two-years of age: consult a physician.

Additional Information:

Store at room temperature.

OTHER INGREDIENTS:

Aloe Barbadensis Leaf (Aloe Vera Gel) Juice, Aqua (Deionized Water), Benzyl Alchol, Caprylic/Capric Triglyceride, Carbomer, Cetearyl Alcohol, Cetereth-20, Cetyl Alcohol, Citrus Aurantifolia (Orange) Oil, Daucus Carota Sativa (Carrot) Extract, Ethylhexylglycerin, Eucalyptus Globulus Oil, Glycerin, 1-Arginine, Lavandula Angustifolia (Lavender) Oil, Lecithin, Methylsulfonylmethane (MSM), Phenoxyethanol, Potassium Hydroxide